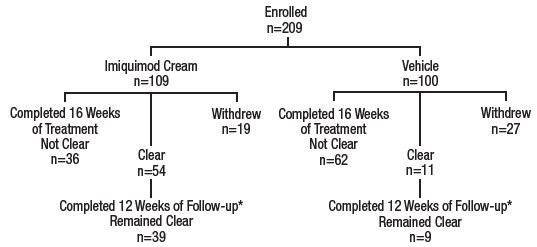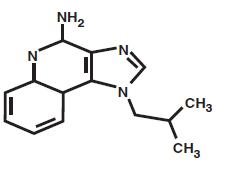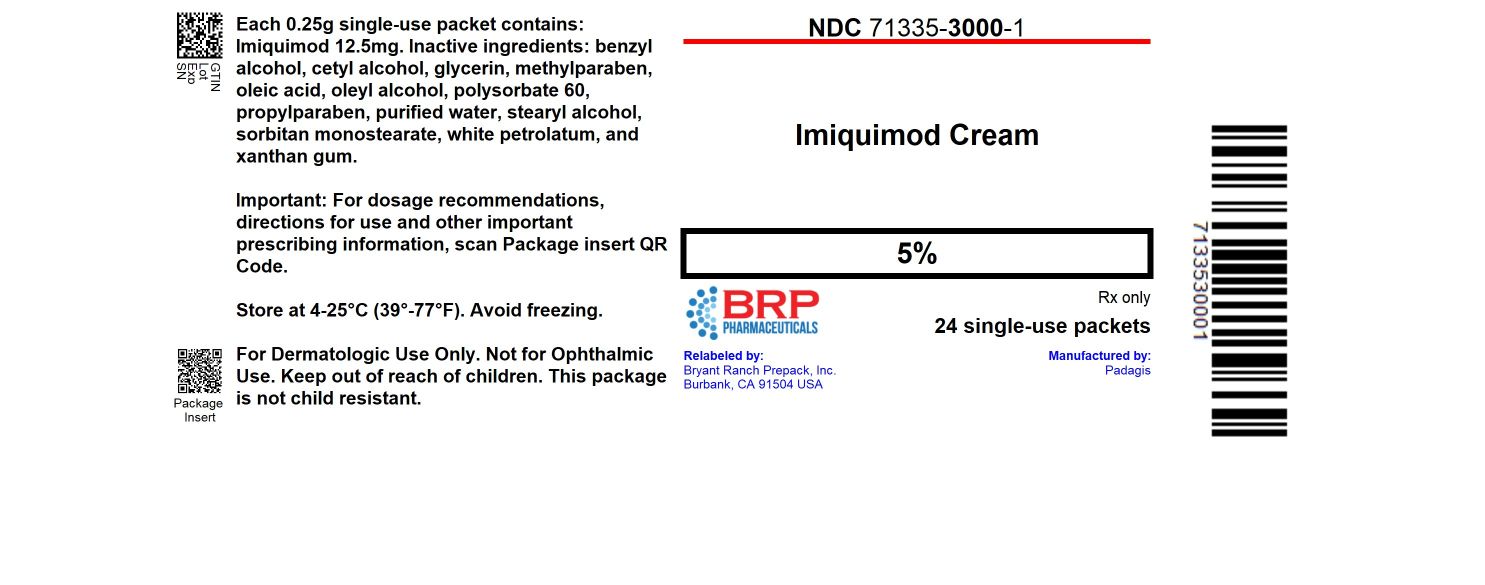 DRUG LABEL: Imiquimod
NDC: 71335-3000 | Form: CREAM
Manufacturer: Bryant Ranch Prepack
Category: prescription | Type: HUMAN PRESCRIPTION DRUG LABEL
Date: 20251105

ACTIVE INGREDIENTS: IMIQUIMOD 12.5 mg/0.25 g
INACTIVE INGREDIENTS: BENZYL ALCOHOL; CETYL ALCOHOL; GLYCERIN; METHYLPARABEN; OLEIC ACID; OLEYL ALCOHOL; POLYSORBATE 60; PROPYLPARABEN; WATER; STEARYL ALCOHOL; SORBITAN MONOSTEARATE; PETROLATUM; XANTHAN GUM

HIGHLIGHTS OF PRESCRIBING INFORMATION

These highlights do not include all the information needed to use IMIQUIMOD CREAM safely and effectively. See full prescribing information for IMIQUIMOD CREAM.
IMIQUIMOD cream, for topical use
Initial U.S. Approval: 1997

RECENT MAJOR CHANGES

Warnings and Precautions, Local Hypopigmentation Reactions (5.2) | 09/2024

1 INDICATIONS AND USAGE

Imiquimod Cream is indicated for the topical treatment of:

• Clinically typical, nonhyperkeratotic, nonhypertrophic actinic keratoses (AK) on the face or scalp in immunocompetent adults. (1.1)

• Biopsy-confirmed, primary superficial basal cell carcinoma (sBCC) in immunocompetent adults with a maximum tumor diameter of 2.0 cm on trunk (excluding anogenital skin), neck, or extremities (excluding hands and feet), only when surgical methods are medically less appropriate and patient follow-up can be reasonably assured. (1.2)

• External genital and perianal warts (EGW) in immunocompetent patients 12 years of age and older. (1.3)

2 DOSAGE AND ADMINISTRATION

- For topical use only; not for oral, ophthalmic, intra-anal or intravaginal use. (2.1)
- AK: Apply once daily before bedtime 2 times per week for a full 16 weeks to a contiguous area of approximately 25 cm^2 on the face or scalp. Apply no more than 1 packet at each application. (2.2)
- sBCC: Apply once daily before bedtime 5 times per week for a full 6 weeks to a target tumor with 2 cm maximum diameter on the trunk (excluding anogenital skin), neck, or extremities (excluding hands and feet). Amount of Imiquimod Cream used based on target tumor diameter. (2.3)
- EGW: Apply thin layer once daily before bedtime 3 times per week until total clearance or for a maximum of 16 weeks. (2.4)

3 DOSAGE FORMS AND STRENGTHS

- Cream: 5% in unit-dose packets. (3)

4 CONTRAINDICATIONS

None. (4)

5 WARNINGS AND PRECAUTIONS

- Local Skin Reactions: Intense local inflammatory reactions can occur (e.g., skin weeping, erosion) Dosage interruption may be required. Severe vulvar swelling may occur and lead to urinary retention; interrupt dosing or discontinue for severe vulvar swelling. (5.1)
- Local Hypopigmentation Reactions: Localized complete depigmentation has occurred and persisted. Discontinue if hypopigmentation develops. (5.2)
- Systemic Reactions: Flu-like systemic signs and symptoms have occurred. Consider dosage interruption for systemic reactions. (5.3)
- Ultraviolet Light Exposure Risks: Avoid or minimize exposure to sunlight and sunlamps. Wear sunscreen and protective clothing. (5.4)

6 ADVERSE REACTIONS

Most common application site or local skin adverse reactions (incidence >28%) are erythema, flaking/scaling/dryness, scabbing/crusting, edema, erosion/ulceration, induration, itching, burning, excoriation, vesicles. Other reported systemic adverse reactions (≥1%): fatigue, fever, and headache. (6.1)

To report SUSPECTED ADVERSE REACTIONS, contact Padagis® at 1-866-634-9120 or FDA at 1-800-FDA-1088 or www.fda.gov/medwatch.

FULL PRESCRIBING INFORMATION

1 INDICATIONS AND USAGE

1.1 Actinic Keratosis

Imiquimod Cream is indicated for the topical treatment of clinically typical, nonhyperkeratotic, nonhypertrophic actinic keratoses (AK) on the face or scalp in immunocompetent adults.

1.2 Superficial Basal Cell Carcinoma

Imiquimod Cream is indicated for the topical treatment of biopsy-confirmed, primary superficial basal cell carcinoma (sBCC) in immunocompetent adults, with a maximum tumor diameter of 2.0 cm, located on the trunk (excluding anogenital skin), neck, or extremities (excluding hands and feet), only when surgical methods are medically less appropriate and patient follow-up can be reasonably assured.

Establish the histological diagnosis of superficial basal cell carcinoma prior to treatment. The safety and effectiveness of Imiquimod Cream have not been established for other types of basal cell carcinomas (BCC), including nodular and morpheaform (fibrosing or sclerosing) types.

1.3 External Genital Warts

Imiquimod Cream is indicated for the topical treatment of external genital and perianal warts (EGW) in immunocompetent patients 12 years of age and older.

2 DOSAGE AND ADMINISTRATION

2.1 Important Dosage and Administration Instructions

Imiquimod Cream is for topical use only. Imiquimod Cream is not for oral, ophthalmic, or intravaginal use. Instruct patients on proper application technique.

Wash hands before and after applying Imiquimod Cream. Wash the treatment area with mild soap and water and allow the area to dry thoroughly (at least 10 minutes) before applying Imiquimod Cream.

If an Imiquimod Cream dose is missed, apply the next dose at the regularly scheduled time.

Avoid contact with the eyes, lips, nostrils, or inside the anus and vagina.

For patients with AK and sBCC, prescribe no more than 3 boxes (36 packets) of Imiquimod Cream for the entire treatment period. For EGW, one packet of Imiquimod Cream contains sufficient cream to cover a wart area of up to 20 cm^2.

Discard partially used packets and do not reuse.

2.2 Dosage and Administration for Actinic Keratosis

Apply Imiquimod Cream topically once daily before bedtime 2 times per week for a full 16 weeks to a defined treatment area of AK on the face or scalp (but not both concurrently). A treatment area is defined as one contiguous area of approximately 25 cm^2 (e.g., 5 cm × 5 cm) on the face (e.g., forehead or one cheek) or on the scalp. Apply Imiquimod Cream to the entire treatment area and rub in until the cream is no longer visible. Apply no more than 1 packet of Imiquimod Cream to the contiguous treatment area at each application. Leave Imiquimod Cream on the skin for approximately 8 hours and then remove with mild soap and water.

For local skin reactions a dosage interruption of several days may be taken if required by the patient's discomfort or severity of the local skin reaction [see Warnings and Precautions (5.1)]. Do not extend treatment beyond 16 weeks due to missed doses or rest periods. Assess response to treatment after resolution of local skin reactions.

2.3 Dosage and Administration for Superficial Basal Cell Carcinoma

Apply Imiquimod Cream topically once daily before bedtime 5 times per week for a full 6 weeks to a biopsy-confirmed sBCC. The target tumor should have a maximum diameter of 2 cm and be located on the trunk (excluding anogenital skin), neck, or extremities (excluding hands and feet). The amount of cream needed to cover the target tumor, including 1 cm of skin surrounding the tumor, is presented in Table 1. Rub Imiquimod Cream into the treatment area until the cream is no longer visible. Leave Imiquimod Cream on the skin for approximately 8 hours and then remove with mild soap and water.

Table 1: Amount of Imiquimod Cream to Use for sBCC

Target Tumor Diameter | Size of Cream Droplet to be Used; (Diameter) | Approximate Amount of Imiquimod Cream to be Used
0.5 to <1.0 cm | 4 mm | 10 mg
≥1.0 to <1.5 cm | 5 mm | 25 mg
≥1.5 to 2.0 cm | 7 mm | 40 mg

For local skin reactions a dosage interruption of several days may be taken if required by the patient's discomfort or severity of the local skin reaction [see Warnings and Precautions (5.1)].

Assess for early clinical clearance after resolution of local skin reactions (e.g., 12 weeks post-treatment). Local skin reactions or other findings (e.g., infection) may require that a patient be seen sooner than the post-treatment assessment for clinical clearance. If there is clinical evidence of persistent tumor at the post-treatment assessment for clinical clearance, consider a biopsy or other alternative intervention. Instruct patients to contact their healthcare provider if any suspicious lesion arises in the treatment area at any time after a determination of clinical clearance [see Clinical Studies (14.2)].

2.4 Dosage and Administration for External Genital Warts

Apply a thin layer of Imiquimod Cream topically once daily before bedtime 3 times per week to EGW until there is total clearance of the genital/perianal warts or for a maximum of 16 weeks. Rub in until the cream is no longer visible. Do not occlude the application site. Leave Imiquimod Cream on the skin for 6 to 10 hours and then remove with mild soap and water.

For local skin reactions, a dosage interruption of several days may be taken if required by the patient's discomfort or severity of the local skin reaction [see Warnings and Precautions (5.1)]. Treatment may resume once the reaction subsides. Nonocclusive dressings such as cotton gauze or cotton underwear may be used to manage skin reactions.

Inform uncircumcised patients treating warts under the foreskin to retract the foreskin and clean the area daily.

Imiquimod Cream may weaken condoms and vaginal diaphragms; therefore, concurrent use is not recommended.

3 DOSAGE FORMS AND STRENGTHS

Cream, 5%: a white to off-white cream in unit-dose packets, with each packet containing 250 mg of cream, equivalent to 12.5 mg of imiquimod.

4 CONTRAINDICATIONS

None.

5 WARNINGS AND PRECAUTIONS

5.1 Local Skin Reactions

Local skin reactions including skin weeping or erosion have been reported with Imiquimod Cream and can occur after a few applications [see Adverse Reactions (6.1)]. Concomitant use of Imiquimod Cream and any other imiquimod products, in the same treatment area, may increase the risk for and severity of local skin reactions.

Imiquimod Cream has the potential to exacerbate inflammatory conditions of the skin, including chronic graft versus host disease.

Severe local inflammatory reactions of the female external genitalia can lead to severe vulvar swelling and urinary retention.

Avoid sexual (genital, anal, oral) contact while Imiquimod Cream is on the skin.

To reduce the risk of local skin reactions and manage local skin reactions that occur with Imiquimod Cream treatment:

- Avoid concomitant use of Imiquimod Cream with any other imiquimod product in the same treatment area.
- Avoid application of Imiquimod Cream to skin that is not intact (i.e., any area with an abrasion, cut, burn, rash, infection, or other condition that has altered skin integrity).
- An interruption of dosing may be required for local skin reactions [see Dosage and Administration (2.2, 2.3, 2.4)]. Interrupt dosing or discontinue Imiquimod Cream for severe vulvar swelling [see Dosage and Administration (2.4)].
- If severe local skin reactions occur, instruct patients to remove Imiquimod Cream by washing the treatment area with mild soap and water.

5.2 Local Hypopigmentation Reactions

Cases of hypopigmentation, including complete depigmentation, were reported during postmarketing use of Imiquimod Cream. In some cases, hypopigmentation and complete depigmentation did not improve or resolve with treatment and persisted for up to 60 months at the time of reporting. Discontinue Imiquimod Cream if hypopigmentation develops.

5.3 Systemic Reactions

Flu-like signs and symptoms have been reported with use of Imiquimod Cream and may accompany, or even precede, local inflammatory reactions [see Adverse Reactions (6.1)]. Signs and symptoms may include malaise, fever, nausea, myalgias, and rigors. Concomitant use of Imiquimod Cream and any other imiquimod products may increase the risk for and severity of systemic reactions. Consider an interruption of dosing if systemic reactions occur.

5.4 Ultraviolet Light Exposure Risks

Imiquimod Cream may cause heightened sunburn susceptibility. Avoid or minimize exposure to sunlight (including sunlamps) during use of Imiquimod Cream. Instruct patients to use sunscreen and wear protective clothing (e.g., a hat). Advise patients not to use Imiquimod Cream until fully recovered from a sunburn.

6 ADVERSE REACTIONS

The following clinically significant adverse reactions are described elsewhere in the labeling:

- Local Skin Reactions [see Warnings and Precautions (5.1)]
- Local Hypopigmentation Reactions [see Warnings and Precautions (5.2)]
- Systemic Reactions [see Warnings and Precautions (5.3)]

6.1 Clinical Trials Experience

Because clinical trials are conducted under widely varying conditions, adverse reaction rates observed in the clinical trials of a drug cannot be directly compared to rates in the clinical trials of another drug and may not reflect the rates observed in practice.

Actinic Keratosis

The data described below reflect exposure to Imiquimod Cream or vehicle in 436 subjects with AK enrolled in two double-blind, vehicle-controlled trials (Studies AK1 and AK2) [see Clinical Studies (14.1)]. Subjects applied Imiquimod Cream, 5% or vehicle topically, to a 25 cm^2 contiguous treatment area on the face or scalp once daily 2 times per week for 16 weeks.

The incidence of selected adverse reactions reported by ≥1% of subjects during the trials is presented in Table 2.

Table 2: Selected Adverse Reactions Occurring in ≥1% of Imiquimod-Treated Subjects with AK and at a Greater Frequency than Vehicle in Studies AK1 and AK2

 | Imiquimod Cream; (n= 215) | Vehicle; (n= 221)
Application Site Reaction | 71 (33%) | 32 (14%)
Upper Respiratory Tract Infection | 33 (15%) | 27 (12%)
Sinusitis | 16 (7%) | 14 (6%)
Headache | 11 (5%) | 7 (3%)
Carcinoma Squamous | 8 (4%) | 5 (2%)
Diarrhea | 6 (3%) | 2 (1%)
Eczema | 4 (2%) | 3 (1%)
Back Pain | 3 (1%) | 2 (1%)
Fatigue | 3 (1%) | 2 (1%)
Fibrillation Atrial | 3 (1%) | 2 (1%)
Infection Viral | 3 (1%) | 2 (1%)
Dizziness | 3 (1%) | 1 (<1%)
Vomiting | 3 (1%) | 1 (<1%)
Urinary Tract Infection | 3 (1%) | 1 (<1%)
Fever | 3 (1%) | 0 (0%)
Rigors | 3 (1%) | 0 (0%)
Alopecia | 3 (1%) | 0 (0%)

The incidence of application site reactions reported by >1% of subjects during the trials is presented in Table 3.

Table 3: Application Site Reactions Reported by >1% of Imiquimod-Treated Subjects with AK and at a Greater Frequency than Vehicle in Studies AK1 and AK2

 | Imiquimod Cream; (n= 215) | Vehicle; (n= 221)
Itching | 44 (20%) | 17 (8%)
Burning | 13 (6%) | 4 (2%)
Bleeding | 7 (3%) | 1 (<1%)
Stinging | 6 (3%) | 2 (1%)
Pain | 6 (3%) | 2 (1%)
Induration | 5 (2%) | 3 (1%)
Tenderness | 4 (2%) | 3 (1%)
Irritation | 4 (2%) | 0 (0%)

Local skin reactions were collected independently of the adverse reaction "application site reaction". The incidence and severity of local skin reactions that occurred during controlled trials are shown in Table 4.

Table 4: Local Skin Reactions in the Treatment Area of Imiquimod-Treated Subjects with AK as Assessed by the Investigator in Studies AK1 and AK2

 | Imiquimod Cream; (n= 215) |  | Vehicle; (n= 220)
 | All Grades* | Severe | All Grades* | Severe
Erythema | 209 (97%) | 38 (18%) | 206 (93%) | 5 (2%)
Flaking/Scaling/Dryness | 199 (93%) | 16 (7%) | 199 (91%) | 7 (3%)
Scabbing/Crusting | 169 (79%) | 18 (8%) | 92 (42%) | 4 (2%)
Edema | 106 (49%) | 0 (0%) | 22 (10%) | 0 (0%)
Erosion/Ulceration | 103 (48%) | 5 (2%) | 20 (9%) | 0 (0%)
Weeping/Exudate | 45 (22%) | 0 (0%) | 3 (1%) | 0 (0%)
Vesicles | 19 (9%) | 0 (0%) | 2 (1%) | 0 (0%)

*Mild, Moderate, or Severe

The adverse reactions that most frequently resulted in clinical intervention (e.g., rest periods, withdrawal from trial) were local skin and application site reactions. In the trials, 2% (5/215) of subjects discontinued for local skin/application site reactions. Of the 215 subjects treated, 35 subjects (16%) on imiquimod cream and 3 of 220 subjects (1%) on vehicle had at least one rest period. Of the imiquimod-treated subjects, 32 (91%) resumed therapy after a rest period.

In the AK trials, 22 of 678 (3.2%) of imiquimod-treated subjects developed treatment site infections that required a rest period off imiquimod cream and were treated with antibiotics (19 with oral and 3 with topical).

Of the 206 imiquimod-treated subjects with both baseline and 8-week post-treatment scarring assessments, 6 (2.9%) had a greater degree of scarring scores at 8 weeks post-treatment than at baseline.

Superficial Basal Cell Carcinoma

The data described below reflect exposure to imiquimod cream or vehicle in 364 subjects with sBCC enrolled in two double-blind, vehicle-controlled trials (sBCC1 and sBCC2) [see Clinical Studies (14.2)]. Subjects applied imiquimod cream, 5% or vehicle topically 5 times per week for 6 weeks.

The incidence of selected adverse reactions reported by ≥1% of subjects during the trials is summarized in Table 5.

Table 5: Selected Adverse Reactions Reported by ≥1% of Imiquimod-Treated Subjects with sBCC and at a Greater Frequency than Vehicle in Studies sBCC1 and sBCC2

 | Imiquimod Cream; (n= 185); N % | Vehicle; (n= 179); N %
Application Site Reaction | 52 (28%) | 5 (3%)
Headache | 14 (8%) | 4 (2%)
Back Pain | 7 (4%) | 1 (<1%)
Upper Respiratory Tract Infection | 6 (3%) | 2 (1%)
Rhinitis | 5 (3%) | 1 (<1%)
Lymphadenopathy | 5 (3%) | 1 (<1%)
Fatigue | 4 (2%) | 2 (1%)
Sinusitis | 4 (2%) | 1 (<1%)
Dyspepsia | 3 (2%) | 2 (1%)
Coughing | 3 (2%) | 1 (<1%)
Fever | 3 (2%) | 0 (0%)
Dizziness | 2 (1%) | 1 (<1%)
Anxiety | 2 (1%) | 1 (<1%)
Pharyngitis | 2 (1%) | 1 (<1%)
Chest Pain | 2 (1%) | 0 (0%)
Nausea | 2 (1%) | 0 (0%)

The most frequently reported adverse reactions were local skin and application site reactions. The incidence of application site reactions reported by >1% of the subjects during the 6-week treatment period is summarized in Table 6.

Table 6: Application Site Reactions Reported by > 1% of Imiquimod-Treated Subjects with sBCC and at a Greater Frequency than Vehicle in Studies sBCC1 and sBCC2

 | Imiquimod Cream; (n= 185) | Vehicle; (n= 179)
Itching | 30 (16%) | 1 (1%)
Burning | 11 (6%) | 2 (1%)
Pain | 6 (3%) | 0 (0%)
Bleeding | 4 (2%) | 0 (0%)
Erythema | 3 (2%) | 0 (0%)
Papule(s) | 3 (2%) | 0 (0%)
Tenderness | 2 (1%) | 0 (0%)
Infection | 2 (1%) | 0 (0%)

Local skin reactions were collected independently of the adverse reaction “application site reaction”. The incidence and severity of local skin reactions that occurred during the controlled trials are shown in Table 7.

Table 7: Local Skin Reactions in the Treatment Area of Imiquimod-Treated Subjects with sBCC as Assessed by the Investigator in Studies sBCC1 and sBCC2

 | Imiquimod Cream; (n= 184) |  | Vehicle; (n= 178)
 | All Grades* | Severe | All Grades* | Severe
Erythema | 184 (100%) | 57 (31%) | 173 (97%) | 4 (2%)
Flaking/Scaling | 167 (91%) | 7 (4%) | 135 (76%) | 0 (0%)
Induration | 154 (84%) | 11 (6%) | 94 (53%) | 0 (0%)
Scabbing/Crusting | 152 (83%) | 35 (19%) | 61 (34%) | 0 (0%)
Edema | 143 (78%) | 13 (7%) | 64 (36%) | 0 (0%)
Erosion | 122 (66%) | 23 (13%) | 25 (14%) | 0 (0%)
Ulceration | 73 (40%) | 11 (6%) | 6 (3%) | 0 (0%)
Vesicles | 57 (31%) | 3 (2%) | 4 (2%) | 0 (0%)

*Mild, Moderate, or Severe

The adverse reactions that most frequently resulted in clinical intervention (e.g., rest periods, withdrawal from trial) were local skin and application site reactions; 10% (19/185) of imiquimod-treated subjects received rest periods. The average number of doses not received per imiquimod-treated subject due to rest periods was 7 doses with a range of 2 to 22 doses; 79% of subjects (15/19) resumed therapy after a rest period. Overall, in the clinical trials, 2% (4/185) of imiquimod-treated subjects discontinued for local skin/application site reactions.

In the sBCC trials, 17 of 1266 (1.3%) imiquimod-treated subjects developed treatment site infections that required a rest period and treatment with antibiotics.

External Genital Warts

In controlled clinical trials for EGW, including a double-blind, vehicle-controlled clinical trial in 209 adult subjects with EGW (Study EGW1) [see Clinical Studies (14.3)], imiquimod cream, 5% was applied topically to EGW in 109 subjects. Selected adverse reactions in imiquimod-treated subjects are listed below (see Table 8).

Table 8: Selected Adverse Reactions in Imiquimod-Treated Subjects with EGW in Vehicle-Controlled Clinical Trials

 | Females |  | Males
 | Imiquimod Cream; (n=117) | Vehicle; (n=103) | Imiquimod Cream; (n=156) | Vehicle; (n=158)
Wart Site
Itching | 38 (32%) | 21 (20%) | 34 (22%) | 16 (10%)
Burning | 30 (26%) | 12 (12%) | 14 (9%) | 8 (5%)
Pain | 9 (8%) | 2 (2%) | 3 (2%) | 1 (1%)
Soreness | 3 (3%) | 0 (0%) | 0 (0%) | 1 (1%)
Fungal Infection | 13 (11%) | 3 (3%) | 3 (2%) | 1 (1%)
Systemic Reactions
Headache | 5 (4%) | 3 (3%) | 8 (5%) | 3 (2%)
Influenza-like Symptoms | 4 (3%) | 2 (2%) | 2 (1%) | 0 (0%)
Myalgia | 1 (1%) | 0 (0%) | 2 (1%) | 1 (1%)

The most frequently reported adverse reactions were local skin and application site reactions.

Overall, 1.2% (4/327) of the subjects discontinued treatment due to local skin/application site reactions.

The incidence and severity of local skin reactions during controlled clinical trials are shown in Table 9.

Table 9: Local Skin Reactions in the Treatment Area of Imiquimod-Treated Subjects with EGW as Assessed by the Investigator in Vehicle-Controlled Clinical Trials

 | Imiquimod Cream |  |  |  | Vehicle
 | Females; (n=114) |  | Males; (n=156) |  | Females; (n=99) |  | Males; (n=157)
 | All Grades* | Severe | All Grades* | Severe | All Grades* | Severe | All Grades* | Severe
Erythema | 74 (65%) | 4 (4%) | 90 (58%) | 6 (4%) | 21 (21%) | 0 (0%) | 34 (22%) | 0 (0%)
Erosion | 35 (31%) | 1 (1%) | 47 (30%) | 2 (1%) | 8 (8%) | 0 (0%) | 10 (6%) | 0 (0%)
Excoriation/; Flaking | 21 (18%) | 0 (0%) | 40 (26%) | 1 (1%) | 8 (8%) | 0 (0%) | 12 (8%) | 0 (0%)
Edema | 20 (18%) | 1 (1%) | 19 (12%) | 0 (0%) | 5 (5%) | 0 (0%) | 1 (1%) | 0 (0%)
Scabbing | 4 (4%) | 0 (0%) | 20 (13%) | 0 (0%) | 0 (0%) | 0 (0%) | 4 (3%) | 0 (0%)
Induration | 6 (5%) | 0 (0%) | 11 (7%) | 0 (0%) | 2 (2%) | 0 (0%) | 3 (2%) | 0 (0%)
Ulceration | 9 (8%) | 3 (3%) | 7 (4%) | 0 (0%) | 1 (1%) | 0 (0%) | 1 (1%) | 0 (0%)
Vesicles | 3 (3%) | 0 (0%) | 3 (2%) | 0 (0%) | 0 (0%) | 0 (0%) | 0 (0%) | 0 (0%)

*Mild, Moderate, or Severe

Remote site skin reactions were also reported. The severe remote site skin reactions reported for females were erythema (3%), ulceration (2%), and edema (1%); and for males, erosion (2%), and erythema, edema, induration, and excoriation/flaking (each 1%).

Other adverse reactions reported by more than 1% of imiquimod-treated subjects included:

Application Site Disorders: hypopigmentation, irritation, rash, sensitivity, stinging, tenderness

Body as a Whole: fatigue, fever

Gastrointestinal System Disorders: diarrhea

Remote Site Reactions: bleeding, burning, itching, pain, tenderness, tinea cruris

6.2 Postmarketing Experience

The following adverse reactions have been identified during post-approval use of imiquimod cream. Because these reactions are reported voluntarily from a population of uncertain size, it is not always possible to reliably estimate their frequency or establish a causal relationship to drug exposure.

Application Site Disorders: tingling at the application site

Body as a Whole: angioedema

Cardiovascular: capillary leak syndrome, cardiac failure, cardiomyopathy, pulmonary edema, arrhythmias (tachycardia, atrial fibrillation, palpitations), chest pain, ischemia, myocardial infarction, syncope

Endocrine: thyroiditis

Gastrointestinal System Disorders: abdominal pain

Hematological: decreases in red cell, white cell, and platelet counts (including idiopathic thrombocytopenic purpura), lymphoma

Hepatic: abnormal liver function

Infections and Infestations: herpes simplex

Musculoskeletal System Disorders: arthralgia

Neuropsychiatric: agitation, cerebrovascular accident, convulsions (including febrile convulsions), depression, insomnia, multiple sclerosis aggravation, paresis, suicide

Respiratory: dyspnea

Urinary System Disorders: proteinuria, dysuria, urinary retention

Skin and Appendages: exfoliative dermatitis, erythema multiforme, hypertrophic scar, hyperpigmentation, hypopigmentation, including complete depigmentation.

Vascular: Henoch-Schönlein purpura syndrome

8 USE IN SPECIFIC POPULATIONS

8.1 Pregnancy

Risk Summary

Available data from case reports and case series of use with imiquimod during pregnancy have not identified a drug-associated risk of major birth defects, miscarriage or adverse maternal or fetal outcomes. There are no controlled or large-scale epidemiologic studies and no exposure registries with imiquimod use in pregnant women.

In animal reproduction studies, there were no adverse developmental effects observed after oral administration of imiquimod in pregnant rats and intravenous administration of imiquimod in pregnant rabbits during organogenesis at doses up to 98 times and 407 times, respectively, the maximum recommended human dose (MRHD) (see Data).

The background risk of major birth defects and miscarriage for the indicated population is unknown. All pregnancies have a background risk of birth defect, loss, or other adverse outcomes. In the U.S. general population, the estimated background risk of major birth defects and miscarriage in clinically recognized pregnancies is 2 to 4% and 15 to 20%, respectively.

Data

Animal Data

The MRHD was set at 2 packets per treatment of Imiquimod Cream (25 mg imiquimod) for the animal multiples of human exposure presented in this label.

Systemic embryofetal development studies were conducted in rats and rabbits. Oral doses of 1, 5, and 20 mg/kg/day imiquimod were administered during the period of organogenesis to pregnant female rats. In the presence of maternal toxicity, fetal effects noted at 20 mg/kg/day (577 times the MRHD based on AUC comparison) included increased resorptions, decreased fetal body weights, delays in skeletal ossification, bent limb bones, and two fetuses in one litter (2 of 1567 fetuses) demonstrated exencephaly, protruding tongues and low-set ears. No treatment-related effects on embryofetal toxicity or malformation were noted at 5 mg/kg/day (98 times the MRHD based on AUC comparison).

Intravenous doses of 0.5, 1, and 2 mg/kg/day imiquimod were administered during the period of organogenesis to pregnant female rabbits. No treatment-related effects on embryofetal toxicity or malformation were noted at 2 mg/kg/day (1.5 times the MRHD based on BSA comparison), the highest dose evaluated in this study, or 1 mg/kg/day (407 times the MRHD based on AUC comparison).

A combined fertility and peri- and postnatal development study was conducted in rats. Oral doses of 1, 1.5, 3, and 6 mg/kg/day imiquimod were administered to male rats from 70 days prior to mating through the mating period and to female rats from 14 days prior to mating through parturition and lactation. No effects on growth, fertility, reproduction, or postnatal development were noted at doses up to 6 mg/kg/day (87 times the MRHD based on AUC comparison), the highest dose evaluated in this study. In the absence of maternal toxicity, bent limb bones were noted in the F1 fetuses at a dose of 6 mg/kg/day (87 times the MRHD based on AUC comparison). This fetal effect was also noted in the oral rat embryofetal development study conducted with imiquimod. No treatment-related malformations were noted at 3 mg/kg/day (41 times the MRHD based on AUC comparison).

8.2 Lactation

Risk Summary

There is no information available on the presence of imiquimod in human milk, the effects of the drug on the breastfed infant, or the effects of the drug on milk production after topical application of Imiquimod Cream to women who are breastfeeding. Systemic concentration following topical administration of imiquimod cream is low; therefore, transfer of Imiquimod Cream into breastmilk is likely to be low [see Clinical Pharmacology (12.3)]. The development and health benefits of breastfeeding should be considered along with the mother’s clinical need for Imiquimod Cream and any potential adverse effects on the breastfed infant from Imiquimod Cream or from the underlying maternal condition.

Clinical Considerations

Avoid application of Imiquimod Cream to areas with increased risk for potential ingestion by or ocular exposure to the breastfeeding child.

8.4 Pediatric Use

Actinic Keratosis and Superficial Basal Cell Carcinoma

The safety and effectiveness of Imiquimod Cream for the treatment of AK or sBCC in pediatric patients have not been established.

External Genital Warts

The safety and effectiveness of Imiquimod Cream for the treatment of EGW in pediatric patients 12 years of age and older have been established. Use of Imiquimod Cream for this indication is supported by evidence from adequate and well controlled trials in adults [see Clinical Studies (14.3)]. The safety and effectiveness of Imiquimod Cream for the treatment of EGW in pediatric patients less than 12 years of age have not been established.

Molluscum Contagiosum

The safety and effectiveness of Imiquimod Cream for the treatment of molluscum contagiosum (MC) in pediatric patients have not been established. Safety and effectiveness of Imiquimod Cream was not demonstrated in two randomized, vehicle-controlled, double-blind trials involving 702 pediatric subjects with MC (470 exposed to Imiquimod Cream; median age 5 years, range 2–12 years).

Adverse reactions reported in pediatric subject with MC (and not previously reported) included otitis media (5% Imiquimod Cream vs. 3% vehicle) and conjunctivitis (3% Imiquimod Cream vs. 2% vehicle).

In a pharmacokinetics trial in subjects aged 2 to 12 years with extensive MC involving at least 10% of total body surface area; among the 20 subjects with evaluable laboratory assessments, the median white blood cell (WBC) count decreased by 1.4 x 10^9/L and the median absolute neutrophil count decreased by 1.42 x 10^9/L.

8.5 Geriatric Use

Of the 215 subjects treated with imiquimod cream in the AK clinical trials, 127 subjects (59%) were 65 years of age or older, while 60 subjects (28%) were 75 years of age or older. Of the 185 subjects treated with imiquimod cream in the sBCC clinical trials, 65 subjects (35%) were 65 years of age or older, while 25 subjects (14%) were 75 years of age or older. No overall differences in safety or effectiveness of Imiquimod Cream have been observed between subjects 65 years of age and older and younger adult subjects.

10 OVERDOSAGE

Topical overdosing of Imiquimod Cream could result in an increased incidence of severe local skin reactions and may increase the risk for systemic reactions.

The most clinically serious adverse reaction reported following multiple oral imiquimod doses of >200 mg (equivalent to imiquimod content of >16 packets of Imiquimod Cream) was hypotension, which resolved following oral or intravenous fluid administration. Consider contacting the Poison Help line (1-800-222-1222) or a medical toxicologist for additional overdosage management recommendations.

11 DESCRIPTION

Imiquimod Cream, 5% is an immune response modifier for topical administration. Each gram contains 50 mg of imiquimod in an off-white oil-in-water vanishing cream base consisting of benzyl alcohol, cetyl alcohol, glycerin, methylparaben, oleic acid, oleyl alcohol, polysorbate 60, propylparaben, purified water, stearyl alcohol, sorbitan monostearate, white petrolatum, and xanthan gum.

Chemically, imiquimod is 1-(2-methylpropyl)-1H-imidazo[4,5-c]quinolin-4-amine. Imiquimod has a molecular formula of C14H16N4 and a molecular weight of 240.3. Its structural formula is:

12 CLINICAL PHARMACOLOGY

12.1 Mechanism of Action

The mechanism of action of Imiquimod Cream in treating AK, sBCC, and EGW lesions is unknown.

12.2 Pharmacodynamics

Actinic Keratosis

In a trial of 18 subjects with AK comparing imiquimod cream to vehicle, increases from baseline in Week 2 biomarker levels were reported for CD3, CD4, CD8, CD11c, and CD68 for imiquimod-treated subjects; however, the clinical relevance of these findings is unknown.

Superficial Basal Cell Carcinoma

An open-label trial in 6 subjects with sBCC suggests that treatment with imiquimod cream may increase the infiltration of lymphocytes, dendritic cells, and macrophages into the tumor lesion; however, the clinical significance of these findings is unknown.

External Genital Warts

Imiquimod has no direct antiviral activity in cell culture. A trial in 22 subjects with EGW comparing imiquimod cream and vehicle shows that imiquimod cream induces mRNA encoding cytokines including interferon-ɑ at the treatment site. In addition, HPVL1 mRNA and HPV DNA are significantly decreased following treatment. However, the clinical relevance of these findings is unknown.

12.3 Pharmacokinetics

Absorption

Systemic absorption of imiquimod across the affected skin of 58 subjects with AK was observed with a dosing frequency of 3 applications per week for 16 weeks. Mean peak serum drug concentrations at the end of Week 16 were approximately 0.1, 0.2, and 3.5 ng/mL for the applications to face (12.5 mg imiquimod, 1 unit-dose packet), scalp (25 mg, 2 packets), and hands/arms (75 mg, 6 packets), respectively.

Table 10: Mean Serum Imiquimod Concentration in Adults Following Administration of the Last Topical Dose during Week 16 (Actinic Keratosis)

Amount of Imiquimod Cream Applied | Mean Peak Serum Imiquimod; Concentration [Cmax]
12.5 mg (1 packet) | 0.1 ng/mL
25 mg (2 packets) | 0.2 ng/mL
75 mg (6 packets) | 3.5 ng/mL

The application surface area was not controlled when more than 1 packet was used. Dose proportionality was not observed. However, it appears that systemic exposure may be more dependent on surface area of application than amount of applied dose. The apparent half-life was approximately 10 times greater with topical dosing than the 2-hour apparent half-life seen following subcutaneous dosing, suggesting prolonged retention of drug in the skin. Mean urinary recoveries of imiquimod and metabolites combined were 0.08% and 0.15% of the applied dose in the group using 75 mg (6 packets) for males and females, respectively following 3 applications per week for 16 weeks.

Systemic absorption of imiquimod was observed across the affected skin of 12 subjects with genital/perianal warts, with an average dose of 4.6 mg. Mean peak drug concentration of approximately 0.4 ng/mL was seen during the trial. Mean urinary recoveries of imiquimod and metabolites combined over the whole course of treatment, expressed as percent of the estimated applied dose, were 0.11% and 2.41% in the males and females, respectively.

13 NONCLINICAL TOXICOLOGY

13.1 Carcinogenesis, Mutagenesis, Impairment of Fertility

In an oral (gavage) rat carcinogenicity study, imiquimod was administered to Wistar rats on a 2 times per week (up to 6 mg/kg/day) or daily (3 mg/kg/day) dosing schedule for 24 months. No treatment-related tumors were noted in the oral rat carcinogenicity study up to the highest doses tested in this study of 6 mg/kg administered 2 times per week in female rats (87 times the MRHD based on weekly AUC comparison), 4 mg/kg administered 2 times per week in male rats (75 times the MRHD based on weekly AUC comparison), or 3 mg/kg administered 7 times per week to male and female rats (153 times the MRHD based on weekly AUC comparison).

In a dermal mouse carcinogenicity study, imiquimod cream (up to 5 mg/kg/application imiquimod or 0.3% imiquimod cream) was applied to the backs of mice 3 times per week for 24 months. A statistically significant increase in the incidence of liver adenomas and carcinomas was noted in high dose male mice compared to control male mice (251 times the MRHD based on weekly AUC comparison). An increased number of skin papillomas was observed in vehicle cream control group animals at the treated site only.

Imiquimod revealed no evidence of mutagenic or clastogenic potential based on the results of five in vitro genotoxicity tests (Ames assay, mouse lymphoma L5178Y assay, Chinese hamster ovary cell chromosome aberration assay, human lymphocyte chromosome aberration assay, and SHE cell transformation assay) and three in vivo genotoxicity tests (rat and hamster bone marrow cytogenetics assay and a mouse-dominant lethal test). Daily oral administration of imiquimod to rats, throughout mating, gestation, parturition, and lactation, demonstrated no effects on growth, fertility or reproduction, at doses up to 87 times the MRHD based on AUC comparison.

14 CLINICAL STUDIES

14.1 Actinic Keratosis

In two double-blind, vehicle-controlled clinical trials, 436 subjects with AK were randomized to treatment with either imiquimod cream, 5% or vehicle applied topically once daily 2 times per week for 16 weeks (Studies AK1 and AK2). The trials enrolled subjects with 4 to 8 clinically typical, visible, discrete, nonhyperkeratotic, nonhypertrophic AK lesions within a 25 cm^2 contiguous treatment area on either the face or scalp. The 25 cm^2 contiguous treatment area could be of any dimensions (e.g., 5 cm × 5 cm, 3 cm × 8.3 cm, 2 cm × 12.5 cm). Trial subjects ranged from 37 to 88 years of age (median 66 years) and 55% had Fitzpatrick skin type I or II. All imiquimod-treated subjects were White.

On a scheduled dosing day, the trial cream was applied to the entire treatment area prior to normal sleeping hours and left on for approximately 8 hours. Twice-weekly dosing was continued for a total of 16 weeks. The clinical response of each subject was evaluated 8 weeks after the last scheduled application of trial cream. Efficacy was assessed by the complete clearance rate, defined as the proportion of subjects at the 8-week post-treatment visit with no (zero) clinically visible AK lesions in the treatment area. Complete clearance included clearance of all baseline lesions, as well as any new or subclinical AK lesions which appeared during therapy.

Complete and partial clearance rates are shown in Table 11. The partial clearance rate was defined as the percentage of subjects in whom 75% or more baseline AK lesions were cleared.

Table 11: Clearance Rates of AK at 8 Weeks Post-Treatment

Complete Clearance Rates (100% AK Lesions Cleared)
Trial | Imiquimod Cream | Vehicle
Study AK1 | 46% (49/107) | 3% (3/110)
Study AK2 | 44% (48/108) | 4% (4/111)
Partial and Complete Clearance Rates
(75% or More Baseline AK Lesions Cleared)
Trial | Imiquimod Cream | Vehicle
Study AK1 | 60% (64/107) | 10% (11/110)
Study AK2 | 58% (63/108) | 14% (15/111)

During treatment, 48% (103/215) of imiquimod-treated subjects experienced an increase in AK lesions relative to the number present at baseline within the treatment area. Subjects with an increase in AK lesions had a similar response to those with no increase in AK lesions.

14.2 Superficial Basal Cell Carcinoma

In two double-blind, vehicle-controlled clinical trials, 364 subjects with primary sBCC were treated with imiquimod cream, 5% or vehicle applied topically once daily 5 times per week for 6 weeks (Studies sBCC1 and sBCC2). Target tumors were biopsy-confirmed sBCC and had a minimum area of 0.5 cm^2 and a maximum diameter of 2.0 cm (4.0 cm^2). Target tumors were not to be located within 1.0 cm of the hairline, or on the anogenital area or on the hands or feet, or to have any atypical features. The population ranged from 31 to 89 years of age (median 60 years) and 65% had Fitzpatrick skin type I or II. On a scheduled dosing day, trial cream was applied to the target tumor and approximately 1 cm (about 1/3 inch) beyond the target tumor prior to normal sleeping hours, and 5 times per week dosing was continued for a total of 6 weeks. The target tumor area was clinically assessed 12 weeks after the last scheduled application of trial cream. The entire target tumor was then excised and examined histologically for the presence of tumor.

Efficacy was assessed by the complete response rate defined as the proportion of subjects with clinical (visual) and histological clearance of the sBCC lesion at 12 weeks post-treatment. Of imiquimod-treated subjects, 6% (11/178) who had both clinical and histological assessments post-treatment, and who appeared to be clinically clear had evidence of tumor on excision of the clinically clear treatment area.

Data on composite clearance (defined as both clinical and histological clearance) are shown in Table 12.

Table 12: Composite Clearance Rates at 12 Weeks Post-Treatment for sBCC

Trial | Imiquimod; Cream | Vehicle
Study sBCC1 | 70% (66/94) | 2% (2/89)
Study sBCC2 | 80% (73/91) | 1% (1/90)
Total | 75% (139/185) | 2% (3/179)

A separate 5-year, open-label trial was conducted to assess the recurrence of sBCC treated with imiquimod cream applied topically once daily 5 days per week for 6 weeks. Target tumor inclusion criteria were the same as for the trials described above. At 12 weeks post-treatment, subjects were clinically evaluated for evidence of persistent sBCC (no histological assessment). Subjects with no clinical evidence of sBCC entered the long-term follow-up period. At the 12-week post-treatment assessment, 90% (163/182) of the subjects enrolled had no clinical evidence of sBCC at their target site and 162 subjects entered the long-term follow-up period for up to 5 years. Two-year (24-month) follow-up data are available from this trial and are presented in Table 13.

Table 13: Estimated Clinical Clearance Rates for sBCC in Imiquimod-Treated Subjects During Follow-up Period in Open-Label Trial

Follow-up Visit after 12-Week Post-Treatment Assessment | No. of Subjects Who Remained Clinically Clear | No. of Subjects with sBCC Recurrence | No. of Subjects Who Discontinued at This Visit with No sBCCa | Estimated Rate of Subjects Who Clinically Cleared and Remained Clearb
Month 3 | 153 | 4 | 5 | 87%
Month 6 | 149 | 4 | 0 | 85%
Month 12 | 143 | 2 | 4 | 84%
Month 24 | 139 | 4 | 0 | 79%

a Reasons for discontinuation included death, noncompliance, entry criteria violations, personal reasons, and treatment of nearby sBCC tumor.

b Estimated rate of subjects who clinically cleared and remained clear are estimated based on the time to event analysis employing the life table method beginning with the rate of clinical clearance at 12 weeks post-treatment.

14.3 External Genital Warts

In a double-blind, placebo-controlled clinical trial, 209 otherwise healthy subjects 18 years and older with EGW were treated with imiquimod cream, 5% or vehicle applied topically once daily 3 times per week for a maximum of 16 weeks (Study EGW1). The median baseline wart area was 69 mm^2 (range 8 to 5525 mm^2). Subject accountability is shown in the figure below.

Figure 1: Subject Accountability for Study EGW1

* The other subjects were either lost to follow-up or experienced recurrences.

Data on complete clearance are listed in Table 14. The median time to complete wart clearance was 10 weeks.

Table 14: Complete Clearance Rates of EGW in Study EGW1

Treatment | Subjects with; Complete; Clearance of Warts | Subjects; Without; Follow-up | Subjects with; Warts Remaining; at Week 16
Overall
Imiquimod Cream (n =109) | 54 (50%) | 19 (17%) | 36 (33%)
Vehicle (n =100) | 11 (11%) | 27 (27%) | 62 (62%)
Females
Imiquimod Cream (n =46) | 33 (72%) | 5 (11%) | 8 (17%)
Vehicle (n =40) | 8 (20%) | 13 (33%) | 19 (48%)
Males
Imiquimod Cream (n =63) | 21 (33%) | 14 (22%) | 28 (44%)
Vehicle (n =60) | 3 (5%) | 14 (23%) | 43 (72%)

16 HOW SUPPLIED/STORAGE AND HANDLING

Imiquimod Cream, 5%, is supplied in single-use packets which contain 250 mg of the cream.

Available as: a box of 24 packets (NDC 71335-3000-01)

Store at 4°-25°C (39°-77°F). Avoid freezing.

Keep out of reach of children.

Repackaged/Relabeled by:
Bryant Ranch Prepack, Inc.
Burbank, CA 91504

17 PATIENT COUNSELING INFORMATION

Advise the patient to read the FDA-approved patient labeling (Patient Information).

Important Administration Instructions

Inform all patients of the following: [see Dosage and Administration (2.1)]

- Imiquimod Cream is for topical use only; avoid contact with the eyes, lips, nostrils, or inside the anus and vagina.
  Instruct patients to rinse their mouth or eyes with water right away if contact with these areas occur.
- Wash hands before and after applying Imiquimod Cream.
- If an Imiquimod Cream dose is missed, apply the next dose at the regularly scheduled time.
- Discard and do not reuse partially used packets.

Inform patients with EGW of the following [see Dosage and Administration (2.4)]:

- Uncircumcised patients treating warts under the foreskin should retract the foreskin and clean the area daily.
- Imiquimod Cream may weaken condoms and vaginal diaphragms; therefore, concurrent use is not recommended.
- Avoid sexual (genital, anal, oral) contact while Imiquimod Cream is on the skin.
- Do not bandage or otherwise occlude the treatment area.

Lactation

Advise breastfeeding women to avoid application of Imiquimod Cream to areas with increased risk for potential ingestion by or ocular exposure to the breastfeeding child [see Use in Specific Populations (8.2)].

Local Skin Reactions

Inform patients of the following [see Dosage and Administration (2.2, 2.3, 2.4) and Warnings and Precautions (5.1)]:

- Local skin reactions may occur during treatment with Imiquimod Cream, ranging from mild to severe in intensity and extending beyond the application site onto the surrounding skin, and may require an interruption of dosing.
- For female patients being treated for EGW, apply Imiquimod Cream at the opening of the vagina, avoiding intravaginal application because local skin reactions may cause difficulty in passing urine.
- If severe local skin reactions occur, remove Imiquimod Cream by washing the treatment area with mild soap and water.
- Contact their healthcare provider promptly if they experience any sign or symptom at the application site that restricts or prohibits their daily activity or makes continued application of Imiquimod Cream difficult.
- Because of local skin reactions, during treatment and until healed, the treatment area is likely to appear noticeably different from normal skin.

Local Hypopigmentation Reactions

Inform patients that cases of hypopigmentation, including complete depigmentation, were reported during postmarketing use of Imiquimod Cream and, in some cases, hypopigmentation and complete depigmentation did not improve or resolve with treatment and persisted for up to 60 months at the time of reporting. Advise patient to inform their healthcare provider if hypopigmentation is observed [see Warnings and Precautions (5.2)].

Systemic Reactions

Inform patients that they may experience flu-like systemic signs and symptoms during treatment with Imiquimod Cream and these symptoms may require an interruption of dosing [see Warnings and Precautions (5.3)].

Ultraviolet Light Exposure Risks

Instruct patients to avoid or minimize exposure to natural or artificial sunlight (tanning beds or UVA/B treatment) while using Imiquimod Cream. Instruct patients to use sunscreen and to wear protective clothing, and to not use Imiquimod Cream if sunburned [see Warnings and Precautions (5.4)].

Manufactured by Padagis®
Yeruham, Israel
www.padagis.com

Rev 01-25
2H100 RC PH8

Patient Information

Imiquimod (i-mi-KWI-mod) Cream, 5%

Important: For use on the skin only (topical). Do not use Imiquimod Cream in your mouth, eyes or vagina.

What is Imiquimod Cream?

Imiquimod Cream is a prescription medicine used on the skin (topical) to treat:

• actinic keratosis on the face or scalp in adults with normal immune systems.

• a type of skin cancer called superficial basal cell carcinoma in adults with normal immune systems when surgery is not an option.

• warts on the outside of the genitals (external) and around the outside of the anus (perianal) in people 12 years and older.

It is not known if Imiquimod Cream is safe and effective in the treatment of:

• people who have weakened immune system.

• people with basal cell nevus syndrome or extreme sensitivity to sunlight (xeroderma pigmentosum).

It is not known if Imiquimod Cream is safe and effective for the treatment of actinic keratosis or superficial basal cell carcinoma in children less than 18 years of age.

It is not known if Imiquimod Cream is safe and effective for the treatment of external genital and perianal warts in children below the age of 12.

Before using Imiquimod Cream, tell your healthcare provider about all of your medical conditions, including if you:

• have problems with your immune system, including long-lasting (chronic) graft versus host disease.

• are being treated or have been treated with other medicines or surgery. You should not use Imiquimod Cream until your skin has healed from other treatments.

• have other skin problems or sunburn.

• are pregnant or plan to become pregnant. It is not known if Imiquimod Cream can harm your unborn baby.

• are breastfeeding or plan to breastfeed. It is not known if imiquimod passes into your breast milk. If you breastfeed during treatment with Imiquimod Cream, avoid contact of your treated skin with your baby’s mouth or eyes. Talk to your healthcare provider about the best way to feed your baby if you use Imiquimod Cream.

Tell your healthcare provider about all the medicines you take, including prescription and over-the-counter medicines, vitamins and herbal supplements.

How should I use Imiquimod Cream?

• Use Imiquimod Cream exactly as prescribed by your healthcare provider.

• Your healthcare provider should show you how to apply Imiquimod Cream.

• Apply Imiquimod Cream just before your bedtime.

• Do not use more Imiquimod Cream than you need to cover the affected area. Using too much Imiquimod Cream, or using it too often, or for too long can increase your chances for having a severe skin reaction or other side effect.

• After applying Imiquimod Cream, the opened packet should be thrown away even if all the Imiquimod Cream was not used.

When using Imiquimod Cream for actinic keratosis:

• Apply Imiquimod Cream 2 times per week for 16 weeks. Examples of 2 times per week application schedules are Monday and Thursday, or Tuesday and Friday.

• Imiquimod Cream should be left on the treated area for about 8 hours. After this time, wash the treated area with mild soap and water to remove Imiquimod Cream.

When using Imiquimod Cream for superficial basal cell carcinoma:

• Apply Imiquimod Cream 1 time a day, for 5 days a week, for example Monday through Friday. Treatment with Imiquimod Cream should continue for 6 full weeks, even if the superficial basal cell carcinoma appears to be gone.

• Apply Imiquimod Cream to the superficial basal cell carcinoma and to 1 centimeter (cm) of skin surrounding the treatment area.

• Imiquimod Cream should be left on the treated area for about 8 hours. After this time, wash the treated area with mild soap and water to remove Imiquimod Cream.

When using Imiquimod Cream for external or perianal warts:

• Apply Imiquimod Cream 3 times per week. Examples of 3 times per week application schedules are Monday, Wednesday and Friday, or Tuesday, Thursday, and Saturday.

• Treatment with Imiquimod Cream should continue until there is complete clearance of all warts or up to 16 weeks. Imiquimod Cream will not cure your genital or perianal warts. New warts may develop during treatment with Imiquimod Cream.

• Uncircumcised males treating warts under their penis foreskin must pull their foreskin back and clean before treatment, and clean daily during the prescribed weeks of treatment.

• Do not get Imiquimod Cream in the anus when applying to perianal warts.

• Imiquimod Cream should be left on the treated area for 6 to 10 hours. After this time, wash the treated area with mild soap and water.

Applying Imiquimod Cream:

• Wash the area where Imiquimod Cream will be applied with mild soap and water.

• Allow the area to dry for at least 10 minutes.

• Wash your hands well.

• Open a new packet of Imiquimod Cream just before use.

• Apply a thin layer of Imiquimod Cream only to the affected area(s) to be treated.

• Rub Imiquimod Cream in all the way until you cannot see the cream on the affected area(s).

• Wash your hands well after applying Imiquimod Cream.

• After about 8 hours, wash the treated area(s) with mild soap and water.

Do not leave Imiquimod Cream on your skin longer than prescribed.

• If you forget to apply Imiquimod Cream, apply the next dose of Imiquimod Cream at your regularly scheduled time.

• If you get Imiquimod Cream in your mouth or in your eyes, rinse well with water right away.

What should I avoid while using Imiquimod Cream?

• Do not cover the treated site with bandages or other closed dressings. Cotton gauze dressings can be used if needed. Cotton underwear can be worn after treating the genital or perianal area.

• Do not use sunlamps or tanning beds, and avoid sunlight as much as possible during treatment with Imiquimod Cream. Use sunscreen and wear protective clothing if you go outside during daylight.

• Do not have sexual contact including genital, anal, or oral sex when Imiquimod Cream is on your genitals or perianal skin. Imiquimod Cream may weaken condoms and vaginal diaphragms. This means they may not work as well to prevent pregnancy.

What are the possible side effects of Imiquimod Cream?

• Treatment site skin reactions. Skin reactions including drainage (weeping) or breakdown of the outer layer of your skin (erosion) can happen after a few applications of Imiquimod Cream. Swelling outside of the vagina (vulvar swelling) may happen in females. Females should take special care if applying the cream at the opening of the vagina because skin reactions can cause pain or swelling and may cause problems passing urine. If you get skin reactions, wash the treated area with mild soap and water.

Stop Imiquimod Cream right away and call your healthcare provider if you get any skin reactions that affect your daily activities, or that do not go away.

• Flu-like symptoms. Tell your healthcare provider if you get tiredness, fever, nausea, muscle pain, joint pain, and chills.

Your healthcare provider may temporarily stop or completely stop your treatment with Imiquimod Cream if you develop treatment site skin reactions or flu-like symptoms.

If you are using Imiquimod Cream for the treatment of superficial basal cell carcinoma, it is very important to have regular follow-up visits with your healthcare provider to check the area to make sure your skin cancer has not come back.

The most common side effects of Imiquimod Cream are skin reactions at the treatment site including:

• redness

• swelling

• a sore, blister, or ulcer

• burning

• skin that becomes hard or thickened

• changes in skin color that do not always go away

• skin peeling

• itching

• scabbing and crusting

• flaking

• scaling

• dryness

Other side effect of Imiquimod Cream include: headache.

These are not all of the possible side effects of Imiquimod Cream.

Call your doctor for medical advice about side effects.

You may report side effects to FDA at 1-800-FDA-1088.

How do I store Imiquimod Cream?

• Store Imiquimod Cream at 39°F to 77°F (4°C to 25°C).

• Do not freeze.

• Safely throw away Imiquimod Cream that is out of date, unused or partially used.

Keep Imiquimod Cream and all medicines out of reach of children.

General information about the safe and effective use of Imiquimod Cream.

Medicines are sometimes prescribed for purposes other than those in a Patient Information leaflet. Do not use Imiquimod Cream for a condition for which it was not prescribed. Do not give Imiquimod Cream to other people, even if they have the same symptoms you have. It may harm them. You can ask your pharmacist or healthcare provider for information about Imiquimod Cream that is written for the health professionals.

What are the ingredients in Imiquimod Cream?

Active Ingredient: imiquimod

Inactive ingredients: benzyl alcohol, cetyl alcohol, glycerin, methylparaben, oleic acid, oleyl alcohol, polysorbate 60, propylparaben, purified water, stearyl alcohol, sorbitan monostearate, white petrolatum, and xanthan gum.

Manufactured by Padagis®

Yeruham, Israel

www.padagis.com

Rev 01-25 2H100 RC PH8

This Patient Information has been approved by the U.S. Food and Drug Administration.

PACKAGE LABEL

Imiquimod 5% Cream #24